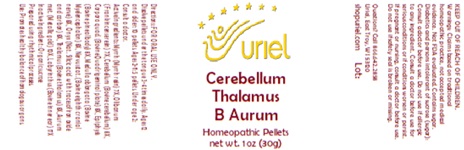 DRUG LABEL: Cerebellum Thalamus B Aurum
NDC: 48951-3264 | Form: PELLET
Manufacturer: Uriel Pharmacy Inc.
Category: homeopathic | Type: HUMAN OTC DRUG LABEL
Date: 20250125

ACTIVE INGREDIENTS: MYRRH 7 [hp_X]/1 1; FRANKINCENSE 7 [hp_X]/1 1; BOS TAURUS CEREBELLUM 8 [hp_X]/1 1; BOS TAURUS BRAIN 8 [hp_X]/1 1; BOS TAURUS PINEAL GLAND 8 [hp_X]/1 1; BOS TAURUS NERVE 8 [hp_X]/1 1; BIFENTHRIN 8 [hp_X]/1 1; SUS SCROFA THALAMUS 8 [hp_X]/1 1; GOLD 10 [hp_X]/1 1; SUS SCROFA EAR 17 [hp_X]/1 1
INACTIVE INGREDIENTS: SUCROSE

Cerebellum Thalamus B Aurum

INDICATIONS AND USAGE

Directions: FOR ORAL USE ONLY.

DOSAGE AND ADMINISTRATION

Dissolve pellets under the tongue 3-4
times daily. Ages 12 and older: 10 pellets.
Ages 2-11: 5 pellets. Under age 2: Consult
a doctor.

ACTIVE INGREDIENT

Active Ingredients: Myrrha (Myrrh resin) 7X, Olibanum (Frankincense resin) 7X, Cerebellum (Bovine cerebellum) 8X, Corpora quad. (Bovine Quadrigeminal plate) 8X, Epiphysis (Bovine pineal body) 8X, Medulla oblongata (Bovine Myelencephalon) 8X, Nervus stat. (Bovine eighth cranial nerve) 8X, Onyx (Nat. Silicic acid with traces of iron oxide and carbon) 8X, Thalamus (Bovine thalamus) 8X, Aurum met. (Metallic gold) 10X, Labyrinthus (Bovine inner ear) 17X

Inactive Ingredient: Organic sucrose

Prepared using rhythmical processes.

PURPOSE

Use: Promotes healthy balance of homologous organs.

KEEP OUT OF REACH OF CHILDREN.

WARNINGS

Warnings: Claims based on traditional homeopathic practice, not accepted medical evidence. Not FDA evaluated. Contains sugar. Diabetics and persons intolerant of sucrose (sugar): Consult a doctor before use. Do not use if allergic to any ingredient. Consult a doctor before use for serious conditions or if conditions worsen or persist. If pregnant or nursing, consult a doctor before use. Do not use if safety seal is broken or missing.

Questions? Call 866.642.2858
Uriel, East Troy, WI 53120
shopuriel.com Lot: